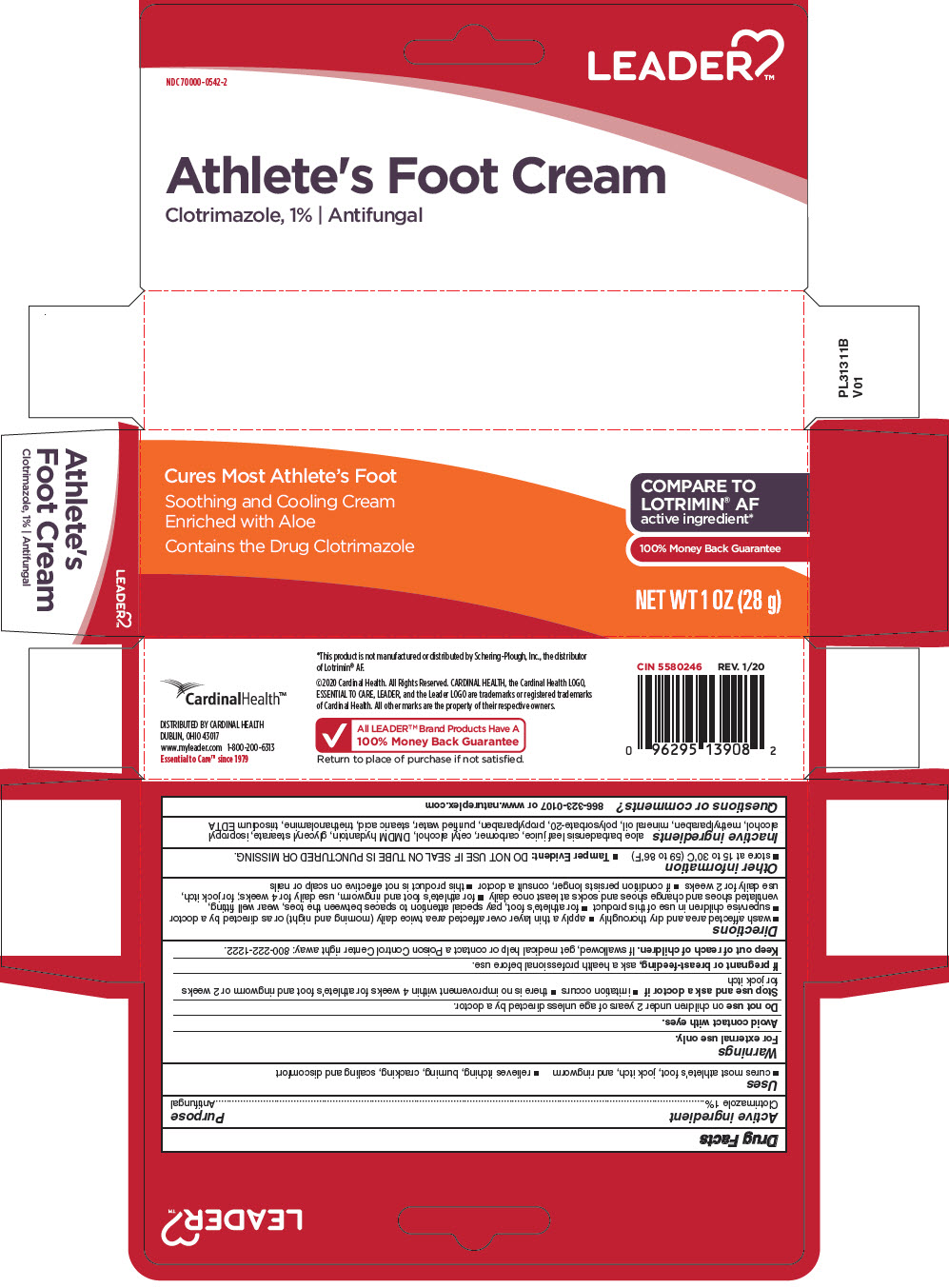 DRUG LABEL: LEADER ATHLETES FOOT CLOTRIMAZOLE
NDC: 70000-0542 | Form: CREAM
Manufacturer: LEADER
Category: otc | Type: HUMAN OTC DRUG LABEL
Date: 20250929

ACTIVE INGREDIENTS: CLOTRIMAZOLE 0.01 g/1 g
INACTIVE INGREDIENTS: ALOE VERA LEAF; CARBOMER HOMOPOLYMER, UNSPECIFIED TYPE; CETYL ALCOHOL; DMDM HYDANTOIN; GLYCERYL MONOSTEARATE; ISOPROPYL ALCOHOL; METHYLPARABEN; MINERAL OIL; POLYSORBATE 20; PROPYLPARABEN; WATER; STEARIC ACID; TROLAMINE; EDETATE TRISODIUM

LEADER™ ATHLETE'S FOOT CREAM CLOTRIMAZOLE 1%

Drug Facts

Active ingredient

Clotrimazole 1%

Purpose

Antifungal

Uses

- cures most athlete's foot, jock itch, and ringworm
- relieves itching, burning, cracking, scaling and discomfort

Warnings

For external use only.

Avoid contact with eyes.

Do not use on children under 2 years of age unless directed by a doctor.

Stop use and ask a doctor if

- irritation occurs
- there is no improvement within 4 weeks for athlete's foot and ringworm or 2 weeks for jock itch

PREGNANCY OR BREAST FEEDING

If pregnant or breast-feeding, ask a health professional before use.

Keep out of reach of children. If swallowed, get medical help or contact a Poison Control Center right away: 800-222-1222.

Directions

- wash affected area and dry thoroughly
- apply a thin layer over affected area twice daily (morning and night) or as directed by a doctor
- supervise children in use of this product
- for athlete's foot, pay special attention to spaces between the toes, wear well fitting, ventilated shoes and change shoes and socks at least once daily
- for athlete's foot and ringworm, use daily for 4 weeks; for jock itch, use daily for 2 weeks
- if condition persists longer, consult a doctor
- this product is not effective on scalp or nails

Other information

- store at 15 to 30°C (59 to 86°F)
- Tamper Evident: DO NOT USE IF SEAL ON TUBE IS PUNCTURED OR MISSING.

Inactive ingredients

aloe barbadensis leaf juice, carbomer, cetyl alcohol, DMDM hydantoin, glyceryl stearate, isopropyl alcohol, methylparaben, mineral oil, polysorbate-20, propylparaben, purified water, stearic acid, triethanolamine, trisodium EDTA

Questions or comments?

866-323-0107 or www.natureplex.com

DISTRIBUTED BY CARDINAL HEALTH
DUBLIN, OHIO 43017

PRINCIPAL DISPLAY PANEL - 28 g Tube Carton

LEADER™

NDC 70000-0542-2

Athlete's Foot Cream
Clotrimazole, 1% | Antifungal

Cures Most Athlete's Foot

Soothing and Cooling Cream
Enriched with Aloe

Contains the Drug Clotrimazole

COMPARE TO
LOTRIMIN® AF
active ingredient*

100% Money Back Guarantee

NET WT 1 OZ (28 g)